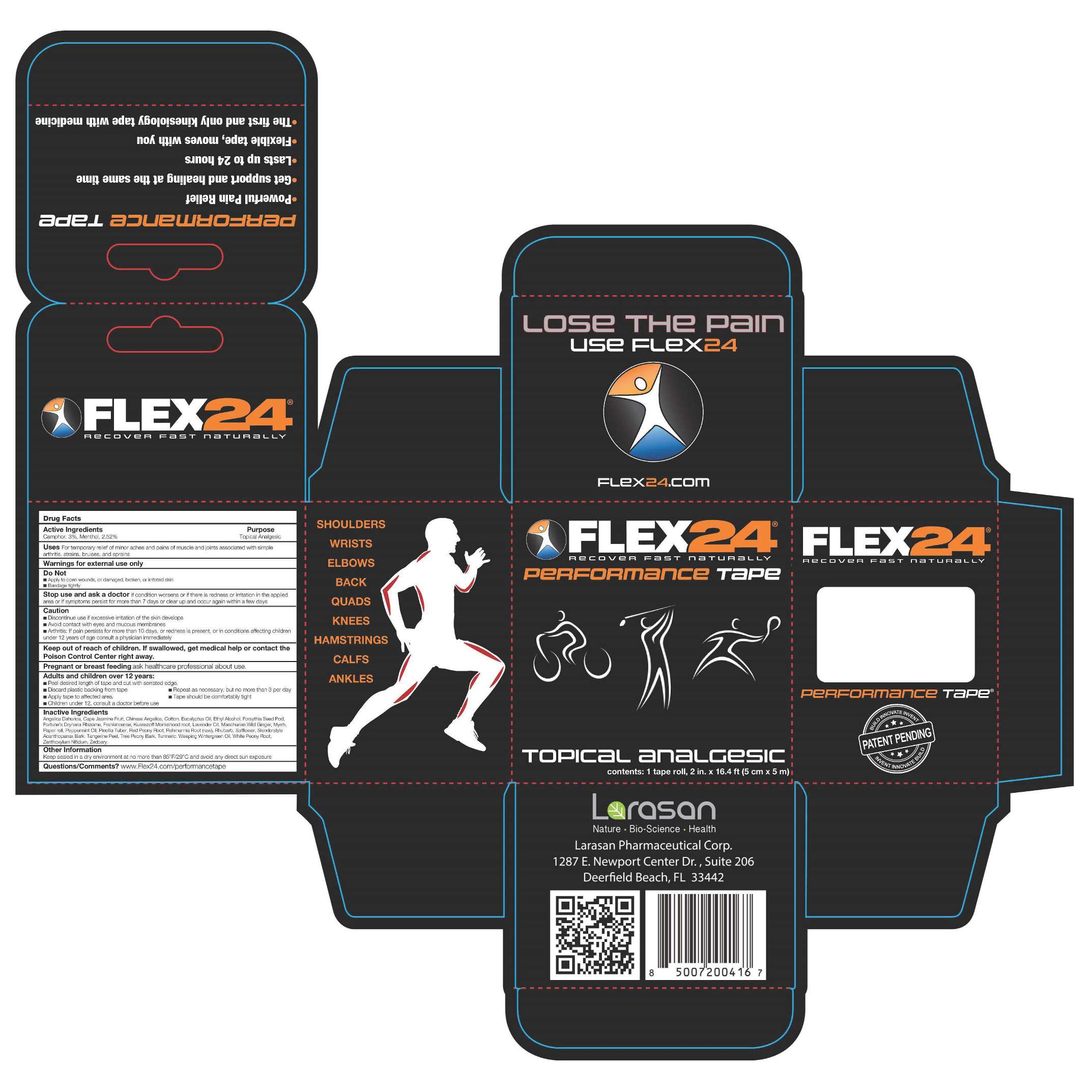 DRUG LABEL: Flex24 Performance
NDC: 54641-007 | Form: PATCH
Manufacturer: Larasan Pharmaceutical Corporation
Category: otc | Type: HUMAN OTC DRUG LABEL
Date: 20170121

ACTIVE INGREDIENTS: CAMPHOR (NATURAL) 3 g/100 g; MENTHOL 2.52 g/100 g
INACTIVE INGREDIENTS: ANGELICA DAHURICA ROOT; GARDENIA JASMINOIDES FRUIT; ANGELICA SINENSIS ROOT; COTTON FIBER; EUCALYPTUS OIL; ALCOHOL; FORSYTHIA SUSPENSA FRUIT; DRYNARIA FORTUNEI ROOT; FRANKINCENSE; ACONITUM KUSNEZOFFII ROOT; LAVENDER OIL; GINGER; MYRRH; PEPPERMINT OIL; PINELLIA TERNATA ROOT; PAEONIA OBOVATA ROOT; REHMANNIA ELATA ROOT; RHUBARB; SAFFLOWER; ELEUTHEROCOCCUS NODIFLORUS ROOT BARK; TANGERINE PEEL; PAEONIA SUFFRUTICOSA ROOT BARK; TURMERIC; METHYL SALICYLATE; PAEONIA LACTIFLORA ROOT

Active Ingredients

Camphor, 3%

Menthol, 2.52%

Purpose

Topical analgesic

Uses

For temporary relief of minor aches and pains of muscle and joints associated with simple arthritis, strains, bruises, and sprains

Warnings

For external use only.

Do Not

■ Apply to open wounds, or damaged, broken, or irritated skin
■ Bandage tightly

Stop Use and Ask a Doctor

if condition worsens or if there is redness or irritation in the applied area or if symptoms persist for more than 7 days or clear up and occur again within a few days

Caution

■ Discontinue use if excessive irritation of the skin develops
■ Avoid contact with eyes and mucous membranes
■ Arthritis: If pain persists for more than 10 days, or redness is present, or in conditions affecting children under 12 years of age consult a physician immediately

Pregnancy or Breast Feeding

ask healthcare professional about use.

Keep Out of Reach of Children

If swallowed, get medical help or contact the Poison Control Center right away.

Directions

■ Peel desired length of tape and cut with serrated edge.
■ Discard plastic backing from tape ■ Repeat as necessary, but no more than 3 per day
■ Apply tape to affected area. ■ Tape should be comfortably tight
■ Children under 12, consult a doctor before use

Inactive Ingredients

Angelica Dahurica, Cape Jasmine Fruit, Chinese Angelica, Cotton, Eucalyptus Oil, Ethyl Alcohol, Forsythia Seed Pod,
Fortune’s Drynaria Rhizome, Frankincense, Kusnezoff Monkshood root, Lavender Oil, Manchurian Wild Ginger, Myrrh,
Paper roll, Peppermint Oil, Pinellia Tuber, Red Peony Root, Rehmannia Root (raw), Rhubarb, Safflower, Slenderstyle
Acanthopanax Bark, Tangerine Peel, Tree Peony Bark, Turmeric, Weeping Wintergreen Oil, White Peony Root,
Zanthoxylum Nitidum, Zedoary.

Other Information

Keep sealed in a dry environment at no more than 85°F/29°C and avoid any direct sun exposure.

Questions/Comments?

www.Flex24.com/performancetape

Larasan Pharmaceutical Corp.

1287 E. Newport Center Drive, Suite 206

Deerfield Beach, FL 33442

PACKAGE LABEL

20170117Flex24PerfTape.jpg